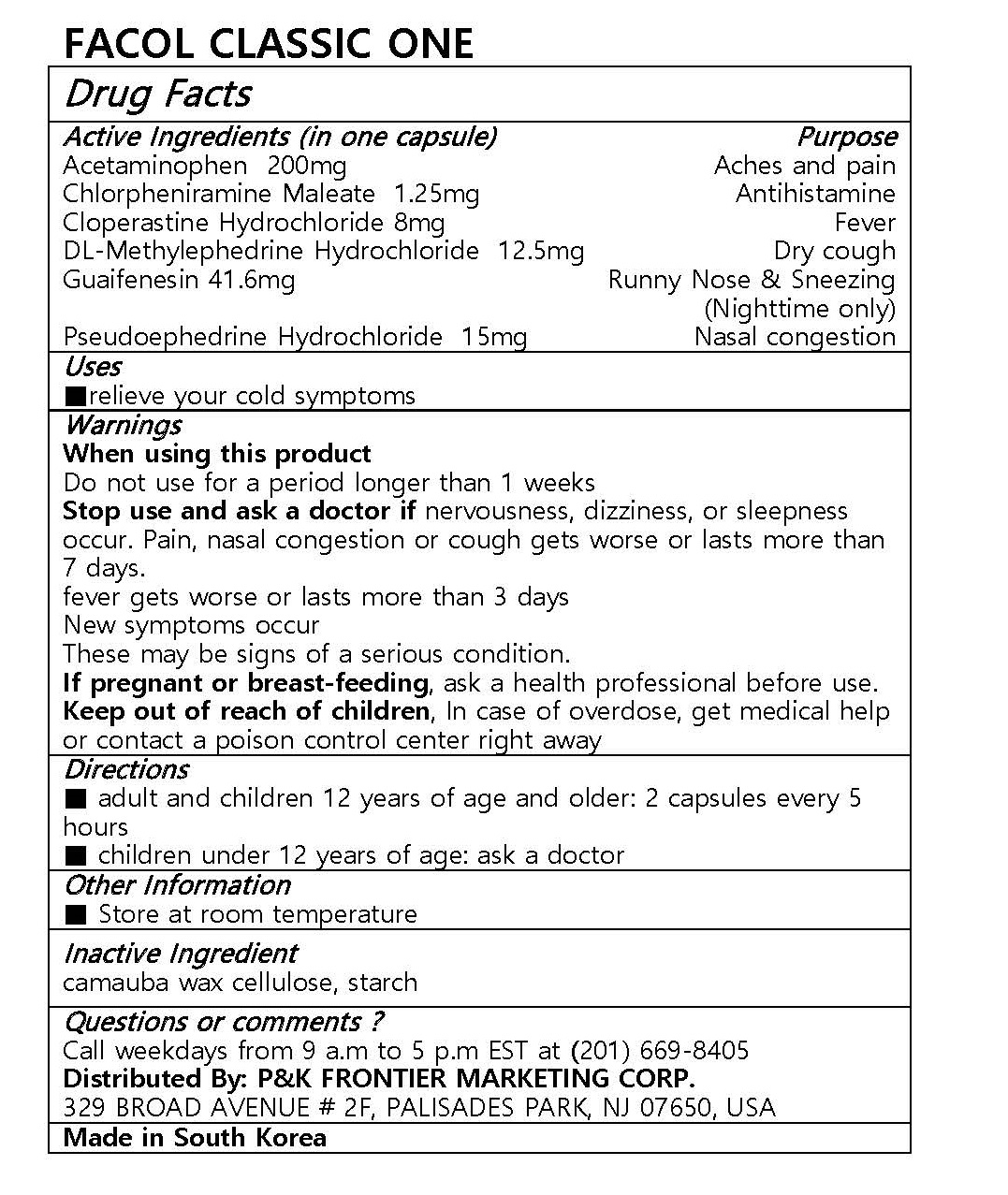 DRUG LABEL: FACOL CLASSIC ONE
NDC: 72689-0013 | Form: CAPSULE
Manufacturer: OASIS TRADING
Category: otc | Type: HUMAN OTC DRUG LABEL
Date: 20181121

ACTIVE INGREDIENTS: ACETAMINOPHEN 200 mg/1 1; GUAIFENESIN 41.6 mg/1 1; PSEUDOEPHEDRINE HYDROCHLORIDE 15 mg/1 1; METHYLEPHEDRINE HYDROCHLORIDE, (+/-)- 12.5 mg/1 1; CLOPERASTINE HYDROCHLORIDE 8 mg/1 1; CHLORPHENIRAMINE MALEATE 1.25 mg/1 1
INACTIVE INGREDIENTS: STARCH, CORN

ACTIVE INGREDIENT

Acetaminophen, Guaifenesin, Pseudoephedrine Hydrochloride, DL-Methylephedrine Hydrochloride, Cloperastine Hydrochloride, Chlorpheniramine Maleate

PURPOSE

relieve your cold symptoms

Keep out of reach of children

INDICATIONS AND USAGE

■ adult and children 12 years of age and older: 2 capsules every 5 hours
■ children under 12 years of age: ask a doctor

Warnings
When using this product
Do not use for a period longer than 1 weeks
Stop use and ask a doctor if nervousness, dizziness, or sleepness occur. Pain, nasal congestion or cough gets worse or lasts more than 7 days.
fever gets worse or lasts more than 3 days
New symptoms occur
These may be signs of a serious condition.
If pregnant or breast-feeding, ask a health professional before use.
Keep out of reach of children, In case of overdose, get medical help or contact a poison control center right away

INACTIVE INGREDIENT

camauba wax cellulose, starch

DOSAGE AND ADMINISTRATION

For oral use only